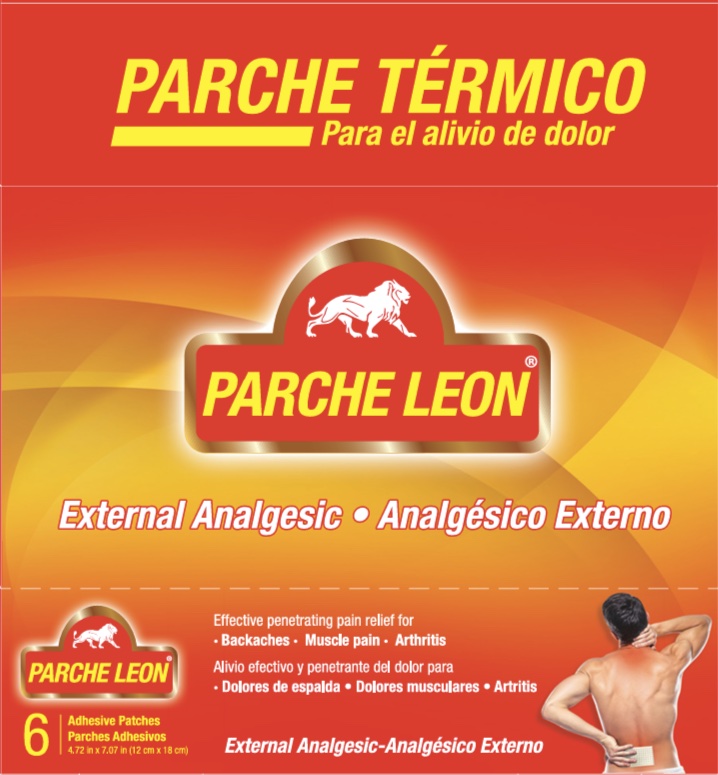 DRUG LABEL: Parche Leon
NDC: 55758-039 | Form: PATCH
Manufacturer: Pharmadel LLC
Category: otc | Type: HUMAN OTC DRUG LABEL
Date: 20250326

ACTIVE INGREDIENTS: CAPSAICIN 0.025 g/1 1; CAMPHOR (SYNTHETIC) 3 g/1 1; MENTHOL, UNSPECIFIED FORM 1.25 g/1 1

Parche Leon Hot (Novamed)

Active ingredients & Purpose

Active ingredients (in each patch) | Purpose
Camphor 3%............................................................. | External analgesic
Menthol 1.25%.......................................................... | External analgesic
Capsaicin 0.025%..................................... | External analgesic

Uses

For temporary relief of minor aches and pains of muscles and joints associated with

- simple back aches
- arthritis
- strains
- bruises
- sprains

Warnings

FOR EXTERNAL USE ONLY. Avoid contact with eyes.

Do not use

- on wounds or damaged skin
- with a tight bandage
- on sensitive skin
- if allergic to any ingredients in this product

Stop use and ask a doctor if

- condition worsens
- symptoms persist for more than 7 days or clear up and occur again within a few days
- redness is present

If pregnant or breast-feeding,

ask a health professional before use.

Keep out of reach of children.

If swallowed, get medical help or contact a Poison Control Center right away.

Directions

- adults and children 12 years of age and older: apply to affected area not more than 3 to 4 times daily
- children under 2 years of age: do not use, consult a doctor
- clean and dry affected area
- remove patch from film
- apply sticky side of patch to affected area
- use one patch at a time
- leave patch on affected area for up to 8-hours at a time

Other information

- store between 59-86°F (15-30°C)
- do not store in direct sunlight or expose to excessive heat
- Do not use if packet containing the patch is torn or broken

Inactive Ingredients

None

Questions or Comments?

1-866-359-3478 (M-F) 9 AM to 5 PM EST or www.pharmadel.com